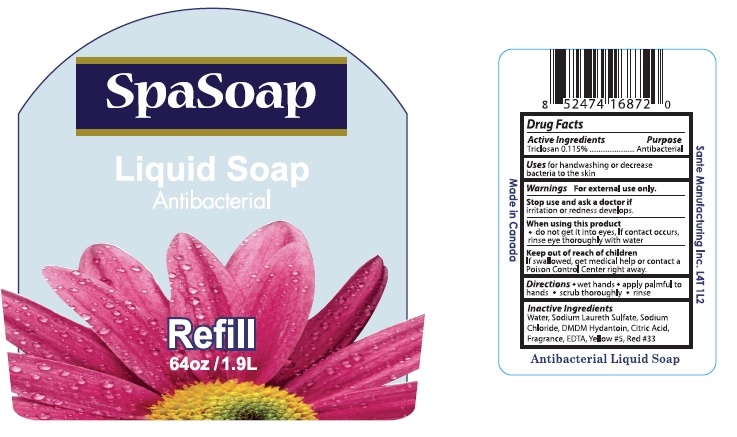 DRUG LABEL: SpaSoap Liquid Antibacterial

NDC: 50157-101 | Form: SOLUTION
Manufacturer: Brands International
Category: otc | Type: HUMAN OTC DRUG LABEL
Date: 20191122

ACTIVE INGREDIENTS: TRICLOSAN 1.15 mg/1 mL
INACTIVE INGREDIENTS: WATER; SODIUM LAURETH SULFATE; SODIUM CHLORIDE; DMDM HYDANTOIN; CITRIC ACID MONOHYDRATE; EDETIC ACID; FD&C YELLOW NO. 5; D&C RED NO. 33

SpaSoap Liquid Antibacterial

Drug Facts

Active Ingredients

Triclosan 0.115%

Purpose

Antibacterial

Uses

for handwashing to decrease bacteria on the skin

Warnings

For external use only.

Stop use and ask a doctor if irritation or redness develops.

When using this product do not get into eyes. If contact occurs, rinse eye thoroughly with water.

Keep out of reach of children. If swallowed, get medical help or contact a Poison Control Center right away.

Directions

- wet hands
- apply palmful to hands
- scrub thoroughly
- rinse

Inactive ingredients

Water, Sodium Laureth Sulfate, Sodium Chloride, DMDM Hydantoin, Citric Acid, Fragrance, EDTA, Yellow # 5, Red # 33

Package Label

SpaSoap

Liquid Soap
Antibacterial
Refill
64 oz / 1.9L
Hand Soap